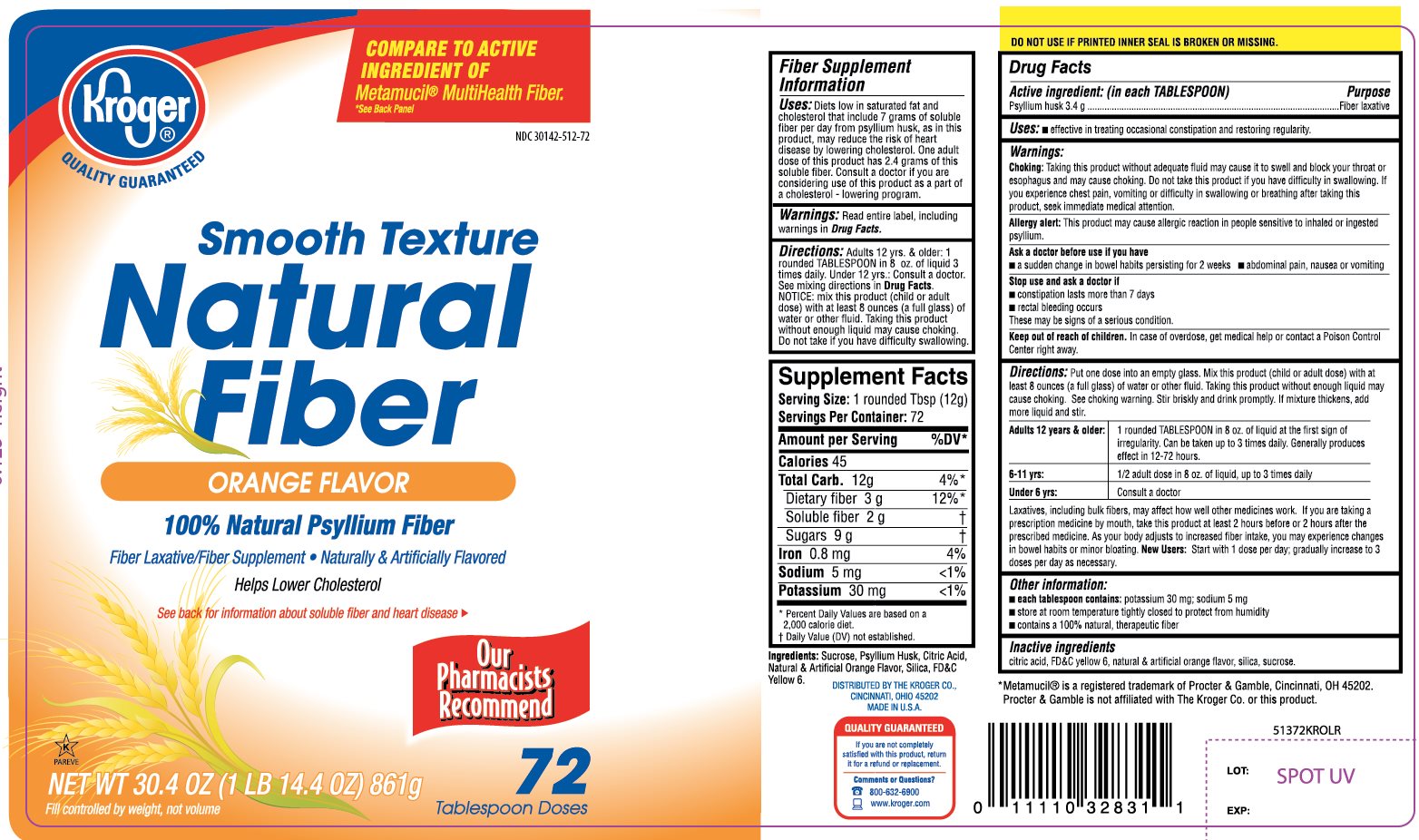 DRUG LABEL: Kroger Natural Fiber
NDC: 30142-512 | Form: POWDER
Manufacturer: KROGER COMPANY
Category: otc | Type: HUMAN OTC DRUG LABEL
Date: 20201016

ACTIVE INGREDIENTS: PSYLLIUM HUSK 3.4 g/12 g
INACTIVE INGREDIENTS: ANHYDROUS CITRIC ACID; FD&C Yellow No. 6; SILICON DIOXIDE; SUCROSE

Kroger Smooth Texture Natural Fiber 72 tablespoon Doses

Drug Facts

Active ingredient: (in each TABLESPOON)

Psyllium husk 3.4 g

Purpose

Fiber Laxative

Uses:

- effective in treating occasional constipation and restoring irregularity

Warnings:

Choking:

Taking this product without adequate fluid may cause it to swell and block your throat or esophagus and may cause choking. Do not take this product if you have difficulty in swallowing. If you experience chest pain, vomiting, or difficulty in swallowing or breathing after taking this product, seek immediate medical attention.

Allergy alert:

This product may cause allergic reaction in people sensitive to inhaled or ingested psyllium.

Ask a doctor before use if you have

- a sudden change in bowel habits persisting for 2 weeks
- abdominal pain, nausea or vomiting

Stop use and ask a doctor if

- constipation lasts more than 7 days
- rectal bleeding occurs

These may be signs of a serious condition.

Keep out of reach of children. In case of overdose, get medical help or contact a Poison Control Center right away at 1-800-222-1222.

Directions:

Put one dose into an empty glass. Mix this product (child or adult dose) with at least 8 ounces (a full glass) of water or other fluid. Taking this product without enough liquid may cause choking. See choking warning. Stir briskly and drink promptly. If mixture thickens, add more liquid and stir.

Adults 12 years & older: | 1 rounded TABLESPOON in 8 ounces of liquid at the first sign of irregularity. Can be taken up to 3 times daily. Generally produces effect in 12-72 hours.
6-11 yrs : | ½ adult dose in 8 ounces of liquid, up to 3 times daily
under 6 yrs: | Consult a doctor

Laxative, including bulk fibers may affect how well other medicines work. If you are taking a prescription medicine by mouth, take this product at least 2 hours before or 2 hours after the prescribed medicine. As your body adjusts to increased fiber intake, you may experience changes in bowel habits or minor bloating.

New Users:

Start with 1 dose per day; gradually increased to 3 doses per day as necessary.

Other information:

- each tablespoon contains: potassium 30 mg; sodium 5 mg
- store at room temperature. Keep the container tightly closed to protect from humidity
- contains a 100% natural, therapeutic fiber

Inactive ingredients:

citric acid, FD&C Yellow No. 6, natural and artificial orange flavor, silica, sucrose.

Questions or comments?

1-800-632-6900

PRINCIPAL DISPLAY PANEL

Kroger®

QUALITY GUARANTEED

NDC 30142-512-72

COMPARE TO ACTIVE INGREDIENT OF Metamucil® MultiHealth Fiber*.

*See Back Panel

Smooth Texture

Natural Fiber

Orange Flavor

100% Natural Psyllium Husk

Fiber Laxative/Fiber Supplement

Naturally and Artificially Flavored

Helps Lower Cholesterol

See back for information about soluble fiber and heart disease.

72 TABLESPOON DOSES‡

NET WT 30.4 OZ (1 LB 14.4 OZ) 861 g

Fill controlled by weight, not volume

Our Pharmacists Recommend

K PAREVE

QUALITY GUARANTEED (if you are not completely satisfied with this product, return it for a refund or replacement.

Comments or Questions?

800-632-6900 www.kroger.com

TAMPER EVIDENT: DO NOT USE IF PRINTED INNER SEAL IS BROKEN OR MISSING

*Metamucil is a registered trademark of Procter & Gamble, Cincinnati, OH 45202. Procter & Gamble is not affiliated with The Kroger Co. or this product.

DISTRIBUTED BY THE KROGER CO.,

CINCINNATI, OHIO 45202

MADE IN U.S.A.